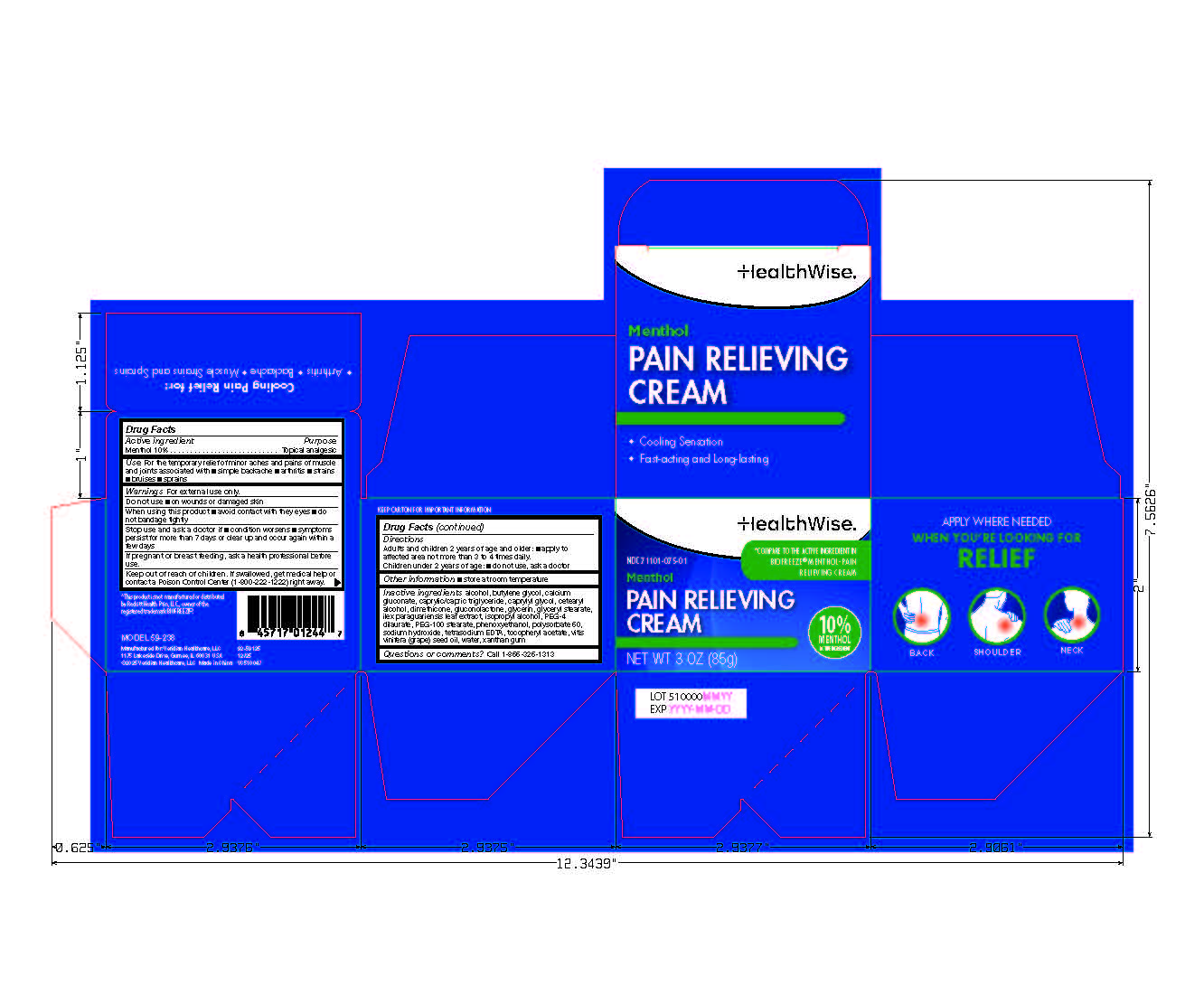 DRUG LABEL: HealthWise Pain Relieving Cream
NDC: 71101-075 | Form: CREAM
Manufacturer: Veridian Healthcare	
Category: otc | Type: HUMAN OTC DRUG LABEL
Date: 20260127

ACTIVE INGREDIENTS: MENTHOL 10 g/100 g
INACTIVE INGREDIENTS: PEG-100 STEARATE; WATER; CAPRYLIC/CAPRIC TRIGLYCERIDE; ALCOHOL; DIMETHICONE; GLYCERYL STEARATE; POLYSORBATE 60; PHENOXYETHANOL; CETOSTEARYL ALCOHOL; XANTHAN GUM; ISOPROPYL ALCOHOL; GLYCERIN; PEG-4 DILAURATE; GRAPE SEED OIL; TETRASODIUM EDTA; SODIUM HYDROXIDE; .ALPHA.-TOCOPHEROL ACETATE; CALCIUM GLUCONATE; BUTYLENE GLYCOL; ILEX PARAGUARIENSIS LEAF; GLUCONOLACTONE; CAPRYLYL GLYCOL

HealthWise Pain Relieving Cream

Active ingredient

Menthol 10%

Purpose

Topical analgesic

Use

Use For the temporary relief of minor aches and pains of muscle and joints associated with

■ simple backache

■ arthritis

■ strains
■ bruises

■ sprains

Warnings

For external use only.

Do not use

on wounds or damaged skin

When using this product

■ avoid contact with they eyes

■ do not bandage tightly

Stop use and ask a doctor if

- condition worsens
- symptoms persist for more than 7 days or clear up and occur again within a few days

If pregnant or breast-feeding,

ask a health professional before use.

Keep out of reach of children.

If swallowed, get medical help or contact a Poison Control Center (800-222-1222) right away.

Directions

Adults and children 2 years of age and older: ■ apply to affected area not more than 3 to 4 times daily.

Children under 2 years of age: ■ do not use, ask a doctor

Other information

Store at room temperature

Inactive ingredients

alcohol, butylene glycol, calcium gluconate, caprylic/capric triglyceride, caprylyl glycol, cetearyl alcohol, dimethicone, gluconolactone, glycerin, glyceryl stearate, ilex paraguariensis leaf extract, isopropyl alcohol, PEG-4 dilaurate, PEG-100 stearate, phenoxyethanol, polysorbate 60, sodium hydroxide, tetrasodium EDTA, tocopheryl acetate, vitis vinifera (grape) seed oil, water, xanthan gum